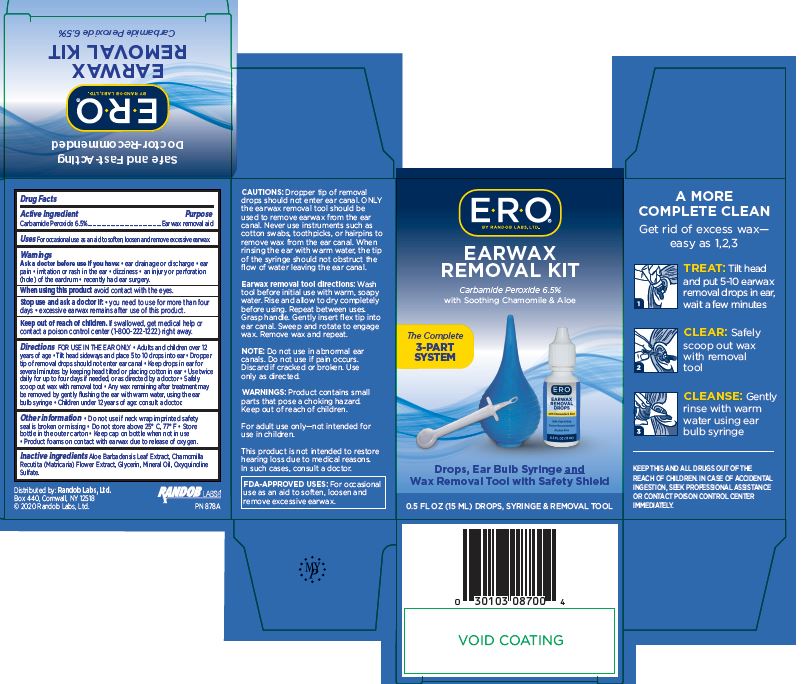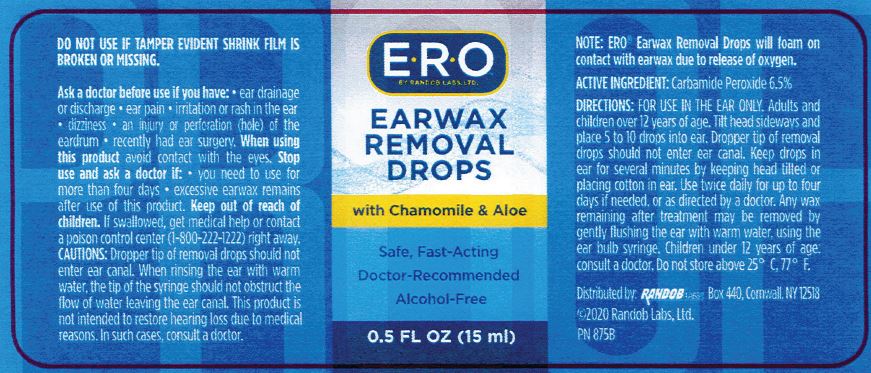 DRUG LABEL: Earwax Removal Drops
NDC: 52412-600 | Form: LIQUID
Manufacturer: Randob Labs, Ltd.
Category: otc | Type: HUMAN OTC DRUG LABEL
Date: 20231219

ACTIVE INGREDIENTS: CARBAMIDE PEROXIDE 0.065 mg/1 mL
INACTIVE INGREDIENTS: CHAMOMILE; OXYQUINOLINE SULFATE; MINERAL OIL; ALOE VERA LEAF; GLYCERIN

ERO Earwax Removal Kit

DOSAGE AND ADMINISTRATION

FOR USE IN THE EAR ONLY

Adults & Children over 12 yrs of age:

Tilt head to the side and place 5-10 drops into ear.

Dropper tip of removal drops should not enter ear canal.

Keep drops in ear for several minutes by keeping head tilted or placing cotton in the ear.

Use twice daily for up to four days if needed, or as directed by a doctor.

Safely scoop out wax with removal tool.

Any wax remaining after treatment may be removed by gently flushing the ear with warm water, using the ear bulb syringe.

Children under 12 yrs of age:

Consult a doctor.

INDICATIONS AND USAGE

For occasional use as an aid to soften, loosen and remove excessive earwax.

PURPOSE

Earwax Removal Aid

ACTIVE INGREDIENT

Carbamide Peroxide 6.5%

INACTIVE INGREDIENT

Aloe Barbadensis Leaf Extract

Chamomilla Recutita (Matricaria) Flower Extract

Glycerin

Mineral Oil

Oxyquinoline Sulfate

Keep out of reach of children. If swallowed, get medical help or contact a Poison Control Center (1-800-222-1212) right away.

When using this product avoid contact with eyes.

Stop use and ask a doctor if:

you need to use more than four days

excessive earwax remains after use of this product

Other Information

Do not use if neck wrap imprinted safety seal is broken or missing

Do not store above 25 degrees C, 77 degrees F

Store bottle in outer carton

Keep cap on bottle when not in use

Product foams on contacy with earwax due to release of oxygen

Warnings

Ask a doctor before use if you have:

ear drainage or discharge

ear pain

irritation, or rash in the ear

dizziness

an injury or perforation (hole) of the eardrum

recently had ear surgery